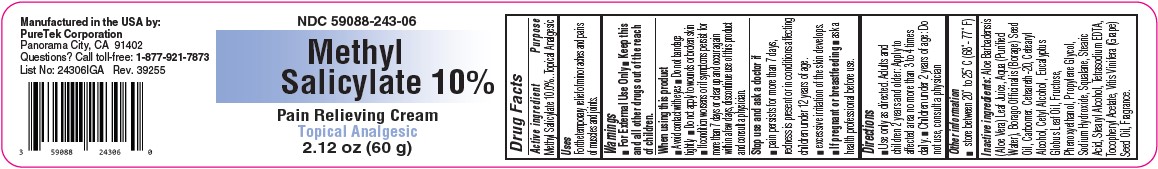 DRUG LABEL: Methyl Salicylate 10%
NDC: 59088-243 | Form: CREAM
Manufacturer: PureTek Corporation
Category: otc | Type: HUMAN OTC DRUG LABEL
Date: 20250612

ACTIVE INGREDIENTS: METHYL SALICYLATE 100 mg/1 g
INACTIVE INGREDIENTS: MENHADEN OIL; PROPYLENE GLYCOL; POLYOXYL 20 CETOSTEARYL ETHER; ALOE VERA LEAF; BORAGE SEED OIL; CARBOMER HOMOPOLYMER TYPE B (ALLYL SUCROSE CROSSLINKED); CETOSTEARYL ALCOHOL; CETYL ALCOHOL; EUCALYPTUS OIL; FRUCTOSE; PHENOXYETHANOL; WATER; SQUALANE; STEARIC ACID; STEARYL ALCOHOL; EDETATE SODIUM; .ALPHA.-TOCOPHEROL ACETATE, DL-; GRAPE SEED OIL; SODIUM HYDROXIDE

NDC 59088-243 Methyl Salicylate 10%

Active ingredients

Methyl Salicylate 10.0%

Purpose

Topical Analgesic

Uses

For the temporary relief of minor aches and pains of muscles and joints.

Warnings

■ For External Use Only

KEEP OUT OF REACH OF CHILDREN

■ Keep this and all other drugs out of the reach of children.

When using this product

■ Avoid contact with eyes ■ Do not bandage tightly ■ Do not apply to wounds or broken skin ■ If condition worsens or if symptoms persist for more than 7 days or clear up and occur again within a few days, discontinue use of this product and consult a physician.

Stop use and ask a doctor if

■ pain persists for more than 7 days, redness is present or in conditions affecting children under 12 years of age. ■ excessive irritation of the skin develops.

PREGNANCY OR BREAST FEEDING

■ If pregnant or breastfeeding ■ ask a health professional before use.

Directions

■ Use only as directed. Adults and children 2 years and older: Apply to affected area no more than 3 to 4 times daily. ■ Children under 2 years of age: Do not use, consult a physician

STORAGE AND HANDLING

■ store between 20° to 25° C (68°- 77° F)

Inactive ingredients

Aloe Barbadensis (Aloe Vera) Leaf Juice, Aqua (Purified Water), Borago Officinalis (Borage) Seed Oil, Carbomer. Ceteareth-20, Cetearyl Alcohol, Cetyl Alcohol , Eucalyptus Globus Leaf Oil, Fructose, Phenoxyethanol, Propylene Glycol, Sodium Hydroxide, Squalane, Stearic Acid, Stearyl Alcohol, Tetrasodium EDTA, Tocopheryl Acetate, Vitis Vinifera (Grape) Seed Oil, Fragrance.

Methyl Salicylate 10%

Manufactured in the USA by:
PureTek Corporation
Panorama City, CA 91402
Questions? Call toll-free: 1-877-921-7873